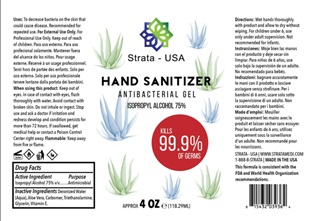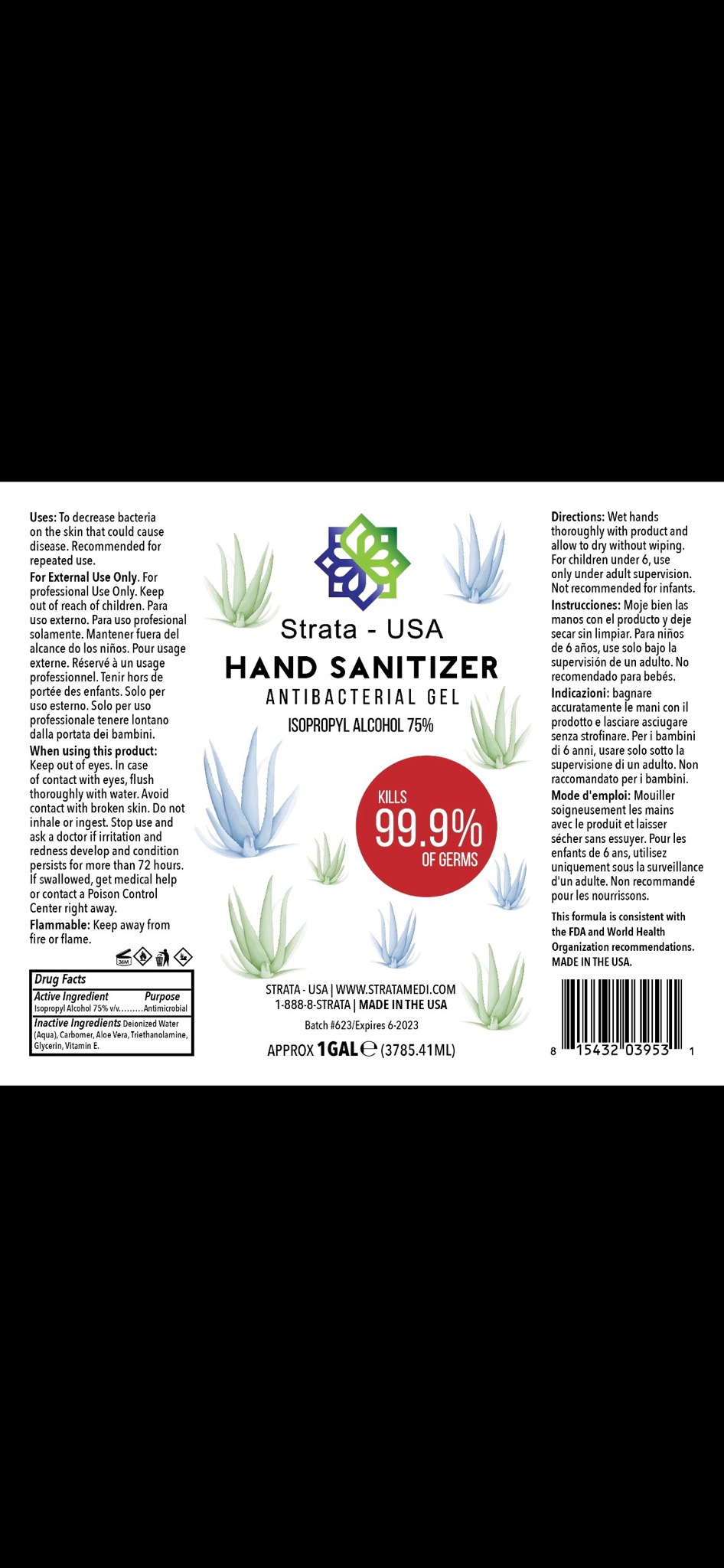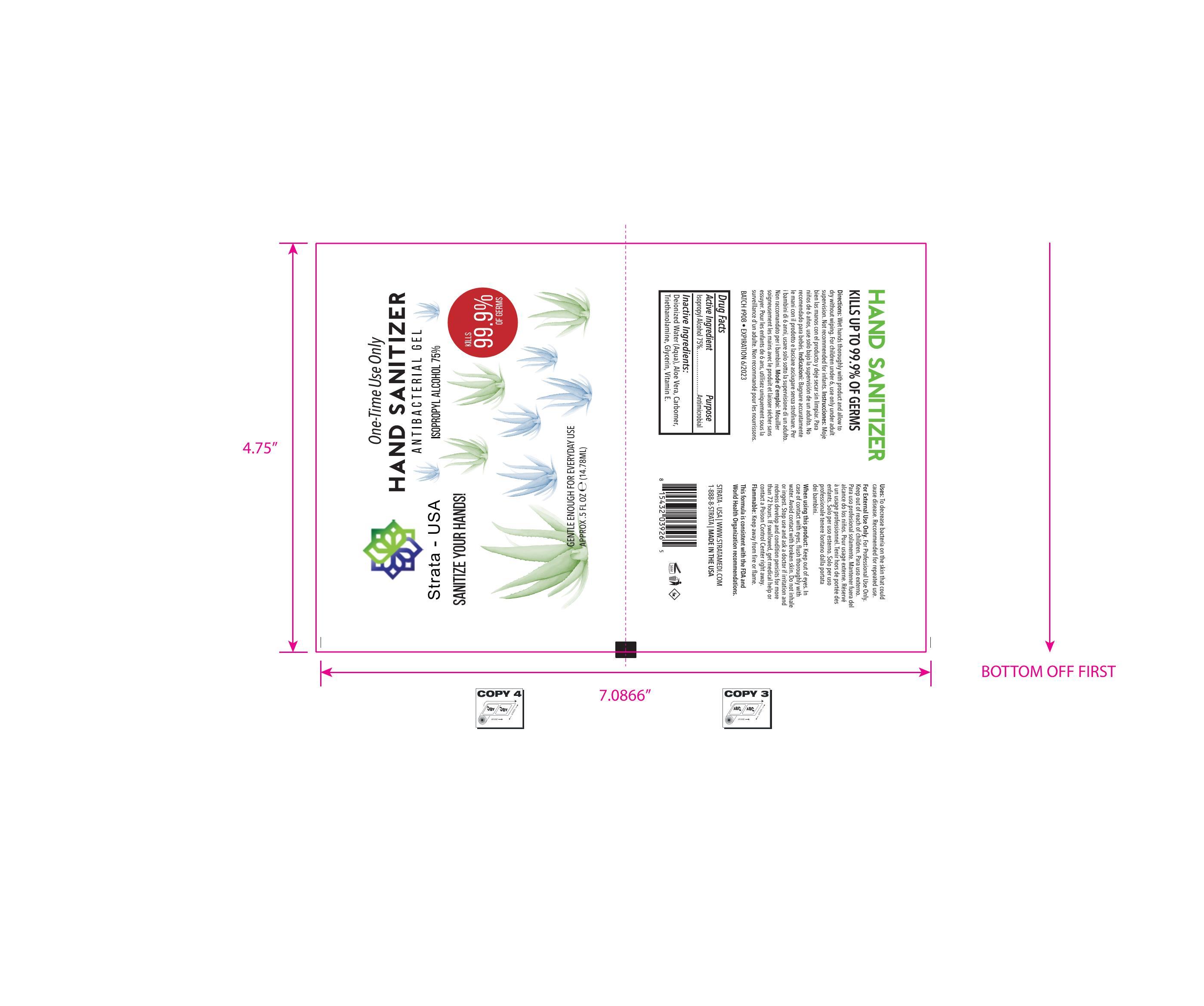 DRUG LABEL: Strata Hand Sanitizer
NDC: 77004-204 | Form: GEL
Manufacturer: Strata USA LLC
Category: otc | Type: HUMAN OTC DRUG LABEL
Date: 20200825

ACTIVE INGREDIENTS: ALCOHOL 75 mL/100 mL
INACTIVE INGREDIENTS: CARBOMER 940 0.3 mL/100 mL; ALOE VERA LEAF 0.2 mL/100 mL; GLYCERIN 0.1 mL/100 mL; WATER 24 mL/100 mL; TROLAMINE 0.1 mL/100 mL

Isopropyl Alcohol 75%

DOSAGE AND ADMINISTRATION

Directions:Wet hands thoroughly with product and allow to dry without wiping. For Children under 6, use only under aduplt supervision. Not recommended for infants. Instrucciones: Mojebien las manos con el producto y deje secar sin limpiar. Para niños de 6 años, use solo bajo la supervisión de un adulto. No recomendado para bebés

PURPOSE

Antimicrobial

ACTIVE INGREDIENT

Isopropyl Alcohol 75%

INACTIVE INGREDIENT

Deionized water (Acqua), Aloe Vera, Carbomer, Triethanolamine, Glycerin, Vitamin E

INDICATIONS AND USAGE

To decrease bacteria on the skin that could cause diseae. Recommended for repeated use

WARNINGS

For External Use Only.

For Professional Use Only. Keep out of reach of children. Para uso externo. Para uso profesional solamente.Mantener fuera del
alcance do los niños. Pour usage externe. Réservé à un usage professionnel. Tenir hors de portée des enfants. Solo per uso esterno. Solo per uso professionale tenere lontano dalla portata dei bambini

When using this product: Keep out of eyes. In case of contact with eyes, ﬂush thoroughly with water. Avoid contact with broken skin. Do not inhale or ingest. Stop use and ask a doctor if irritation and redness develop and condition persists for more than 72 hours. If swallowed, get medical help or contact a Poison Control Center right away. Flammable: Keep away from ﬁre or ﬂame.

Keep out of reach of children

Strata 77004-204-27 4oz 118 ml

NDC77004-20425 0.5 oz 14.78 ml